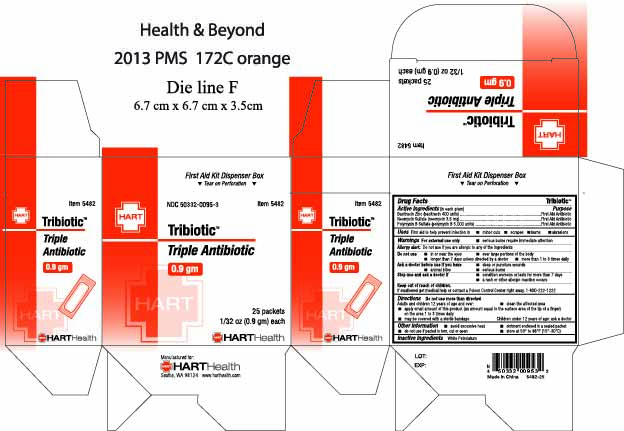 DRUG LABEL: TRIBIOTIC
NDC: 50332-0095 | Form: OINTMENT
Manufacturer: HART Health
Category: otc | Type: HUMAN OTC DRUG LABEL
Date: 20251202

ACTIVE INGREDIENTS: BACITRACIN ZINC 400 [iU]/1 g; NEOMYCIN SULFATE 3.5 mg/1 g; POLYMYXIN B SULFATE 5000 [iU]/1 g
INACTIVE INGREDIENTS: WHITE PETROLATUM

TRIBIOTIC

Active Ingredients (in each gram)

Bacitracin Zinc (bacitracin 400 units)

Neomycin Sulfate (neomycin 3.5mg)

Polymyxin B Sulfate (polymyxin B 5,000 units)

Purpose:

Topical Antibiotic

Topical Antibiotic

Topical Antibiotic

INDICATIONS AND USAGE

Uses: First aid to help prevent infection in

- minor cuts
- scrapes
- burns
- abrasions

Warnings: For external use only

Serious burns require immediate medical attention

Allergy alert: Do not use if you are allergic to any of the ingredients

do not use

- in or near the eyes
- over large portions of the body
- longer than 7 days unless directed by a doctor
- more than 1 to 3 times daily

Ask a doctor before use if you have

- deep or puncture wounds
- animal bites
- serious burns

Stop use and ask a doctor if

- condition worsens or lasts for more than 7 days
- a rash or other allergic reaction occurs

Keep out of reach of children. If swallowed get medical help or contact a Poison Control Center right away. 1-800-222-1222

Directions:

Do not use more than directed.

Adults and children 12 years of age and over:

- clean the affected area
- apply small amount of this product (an amount equal to the surface area of the tip of a finger) on the area 1 to 3 times daily
- may be covered with a sterile bandage

Children under 12 years of age: ask a doctor

Other Information

- avoid excessive heat
- ointment enclosed in a sealed packet
- do not use if packet is torn, cut or open
- store at 59° to 86°F (15°-30°C)

INACTIVE INGREDIENT

White Petrolatum